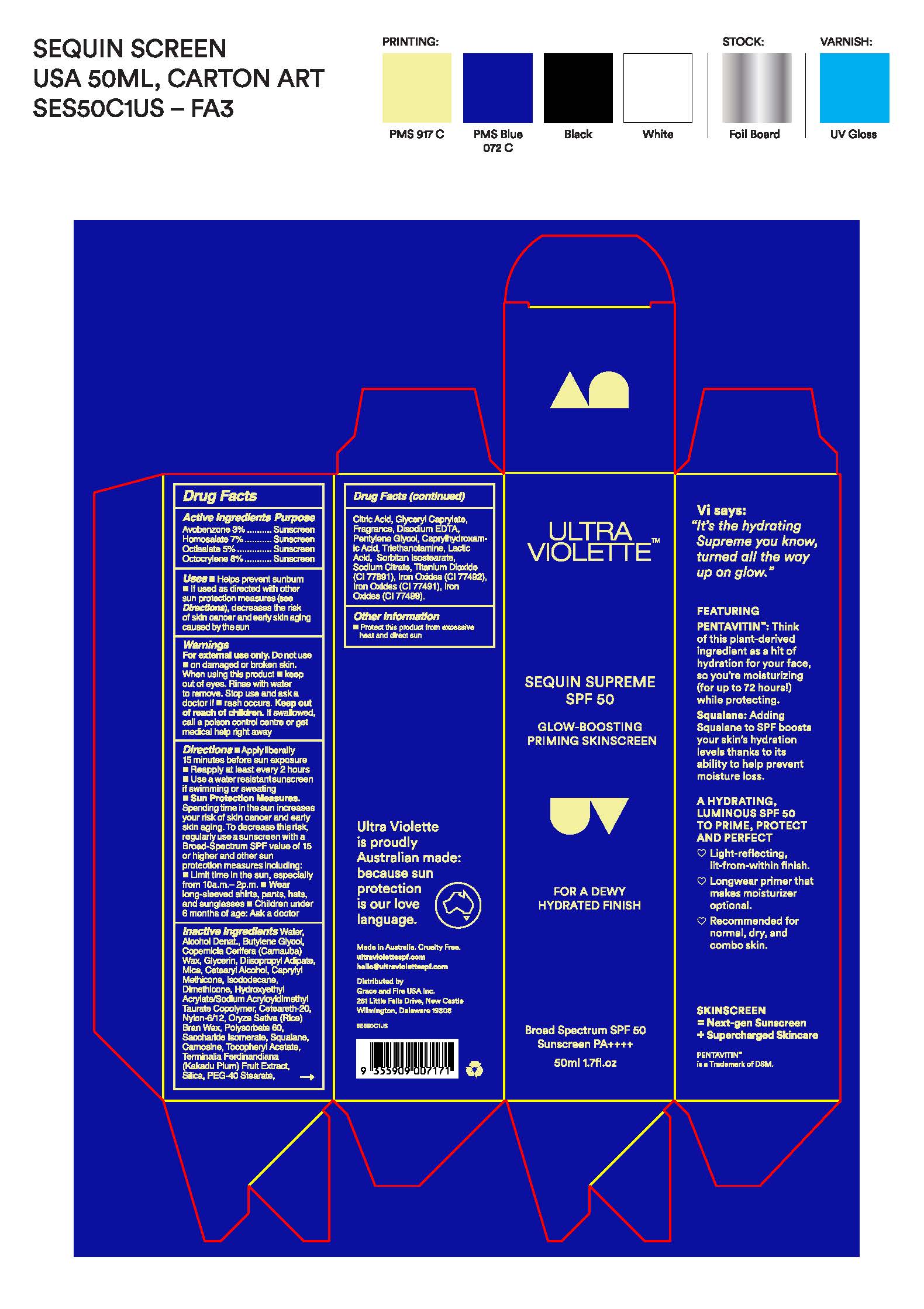 DRUG LABEL: Ultra Violette Sequin Supreme SPF 50
NDC: 84803-107 | Form: LOTION
Manufacturer: Grace and Fire USA Inc.
Category: otc | Type: HUMAN OTC DRUG LABEL
Date: 20251013

ACTIVE INGREDIENTS: AVOBENZONE 30 mg/1 mL; HOMOSALATE 70 mg/1 mL; OCTISALATE 50 mg/1 mL; OCTOCRYLENE 80 mg/1 mL
INACTIVE INGREDIENTS: HYDRATED SILICA 0.25 mg/1 mL; SORBITAN ISOSTEARATE 0.021 mg/1 mL; ALPHA-TOCOPHEROL ACETATE 1.5 mg/1 mL; T-BUTYL ALCOHOL 0.005 mg/1 mL; POLYSORBATE 60 0.07 mg/1 mL; PENTYLENE GLYCOL 0.075 mg/1 mL; CAPRYLHYDROXAMIC ACID 0.05 mg/1 mL; CETEARETH-20 0.5 mg/1 mL; COPERNICIA CERIFERA (CARNAUBA) WAX 1.9 mg/1 mL; PEG-40 STEARATE 0.25 mg/1 mL; CI 77492 0.03 mg/1 mL; DISODIUM EDTA-COPPER 0.1 mg/1 mL; BUTYLENE GLYCOL 2 mg/1 mL; CARNOSINE 0.03 mg/1 mL; TITANIUM DIOXIDE 0.58 mg/1 mL; ORYZA SATIVA (RICE) BRAN 0.1 mg/1 mL; WATER 19.25 mg/1 mL; GLYCERIN 1.77 mg/1 mL; DIISOPROPYL ADIPATE 1.5 mg/1 mL; KAKADU PLUM 0.02 mg/1 mL; CITRIC ACID 0.003 mg/1 mL; HYDROXYETHYL ACRYLATE/SODIUM ACRYLOYLDIMETHYL TAURATE COPOLYMER (100000 MPA.S AT 1.5%) 0.51 mg/1 mL; ALCOHOL 2.49 mg/1 mL; CAPRYLYL METHICONE 1 mg/1 mL; ISODODECANE 1 mg/1 mL; DIMETHICONE 0.75 mg/1 mL; NYLON 612 (18000 MW) 0.5 mg/1 mL; LACTIC ACID 0.025 mg/1 mL; CI 77491 0.008 mg/1 mL; CI 77499 0.0035 mg/1 mL; TRIETHANOLAMINE 0.025 mg/1 mL; CETEARYL ALCOHOL 1 mg/1 mL; MICA 1.42 mg/1 mL; GLYCERYL CAPRYLATE 0.375 mg/1 mL; SQUALANE 0.35 mg/1 mL; SACCHARIDE ISOMERATE 0.31 mg/1 mL; FRAGRANCE 13576 0.075 mg/1 mL

ACTIVE INGREDIENTS

AVOBENZONE 3.0%

HOMOSALATE 7.0%

OCTISALATE 5.0%

OCTOCRYLENE 8.0%

Purpose

SUNSCREEN

USE

HELPS PREVENT SUNBURN

if used as directed with other sun protection measures (see Directions), decreases the risk of skin cancer and early skin aging caused by the sun

WARNINGS SECTION

For External Use Only

Do not use

on damaged or broken skin

WHEN USING

Keep out of eyes. Rinse with water to remove.

Stop use and ask a doctor if

rash occurs

Keep out of reach of children

If swallowed, get medical help or contact a Poison Control Center right away

Directions

Directions for Sunscreen Use

- apply liberally and evenly 15 minutes before sun exposure
- reapply at least every 2 hours
- use a water resistant sunscreen if swimming or sweating
- Sun Protection Measures. Spending time in the sun increases your risk of skin cancer and early skin aging. To decrease this risk, regularly use a sunscreen with a Broad Spectrum SPF value of 15 or higher and other sun protection measures including:
- limit time in the sun, especally from 10 a.m. - 2 p.m.
- wear long-sleeved shirts, pants, hats, and sunglasses
- children under 6 months of age, Ask a doctor

Inactive Ingredients

Water, Alcohol Denat., Butylene Glycol, Copernicia Cerifera (Carnauba) Wax, Glycerin, Diisopropyl Adipate, Mica, Cetearyl Alcohol, Caprylyl Methicone, Isododecane, Dimethicone, Hydroxyethyl Acrylate/Sodium Acryloyldimethyl Taurate Copolymer, Ceteareth-20, Nylon-6/12, Oryza Sativa (Rice) Bran Wax, Polysorbate 60, Saccharide Isomerate, Squalane, Carnosine, Tocopheryl Acetate, Terminalia Ferdinandiana (Kakadu Plum) Fruit Extract, Silica, PEG-40 Stearate, Citric Acid, Glyceryl Caprylate, Fragrance, Disodium EDTA, Pentylene Glycol, Caprylhydroxamic Acid, Triethanolamine, Lactic Acid, Sorbitan Isostearate, Sodium Citrate, Titanium Dioxide (CI 77891), Iron Oxides (CI 77492), Iron Oxides (CI 77491), Iron Oxides (CI 77499).

Other Information

Other information protect the product in this container from excessive heat and direct sun

PRINCIPLE DISPLAY PANEL.

ULTRA

VIOLETTE

SEQUIN SUPREME SPF 50

GLOW -BOOSTING

PRIMING SUNSCREEN

UV

FOR A DEWY

HYDRATED FINISH

Broad Spectrum SPF 50

Sunscreen PA++++

50ml 1.7fl.oz